DRUG LABEL: Zantanol Tab.
NDC: 58354-101 | Form: TABLET
Manufacturer: Cho-A Pharm.Co.,Ltd.
Category: otc | Type: HUMAN OTC DRUG LABEL
Date: 20170228

ACTIVE INGREDIENTS: MAGNESIUM OXIDE 50 mg/424 mg; MAGALDRATE 50 mg/424 mg
INACTIVE INGREDIENTS: ALMASILATE; RANITIDINE HYDROCHLORIDE; LOW-SUBSTITUTED HYDROXYPROPYL CELLULOSE (8% HYDROXYPROPYL: 140000 MW); CROSPOVIDONE, UNSPECIFIED; HYDROXYPROPYL CELLULOSE, UNSPECIFIED; MAGNESIUM STEARATE; water

Zantanol Tab.

Active Ingredients

Magnesium Aluminum Hydrate 100mg

Magnesium Oxide 50mg

Purpose

Antacid

Keep out of reach of children

• In case of overdose, get medical help or contact a Poison Control Center (1-800-222-1222) right away.

Uses

Helps relieve symptoms associated with indigestion: pain in the upper abdomen, heartburn, indigestion, nausea.

Warnings

For oral use only

Use only the recommended dosage

Do not use if you have
• hemodyscrasia
• kidney, liver, bowel, stomach, and duodenum disease
• immunological disorder (asthma,rheumatism)
• previously experienced sensitivity to this medication
• dialysis

Do not use if the user under 15 and over 80 years old.

When using this product
• do not take other stomach medicine.
• do not take alcohol

Ask a doctor, dentist, or pharmacist before use if the user
• take other medication
• take medical treatment
• have allergic reaction for drug
• are over 65 years old
• have sore throat, cough, or fever
• are having continuously stomachaches
• have kidney disease

If pregnant or breast-feeding, ask a health professional before use.

Store at cool temperature and dry place with a closed container. Avoid direct sunlight. - Store in a container other than its original container is equivalent to misuse. In order to prevent the reduction of drug efficacy, keep the product in its original container for storage.

Directions

• do not take more than the recommended dose
• adults (over 15 and under 80 years old): take 2 tablets per session. After 5 hours if symptoms last 0.5-1g per session, 1-3 times per day, before meal. Do not take over 4 tablets a day.

Inactive Ingredients

Ranitidine Hydrochloride, Magnesium Aluminosilicate, Low Substituted Hydroxypropylcellulose, Crospovidone, Hydroxypropylcellulose, Magnesium Stearate, Opadry white 80W68912, Purified Water